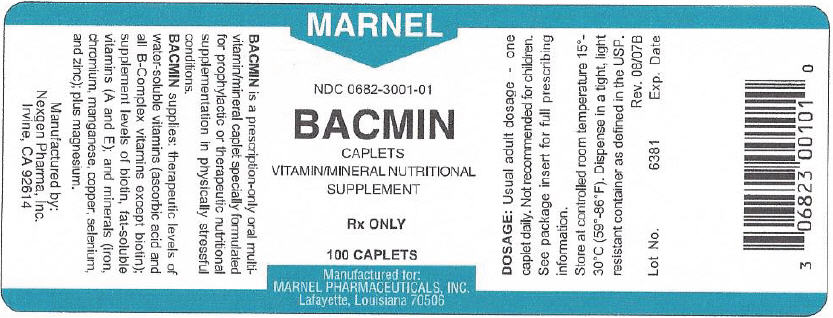 DRUG LABEL: BACMIN
NDC: 0682-3001 | Form: TABLET, COATED
Manufacturer: Marnel Pharmaceuticals, Inc.
Category: prescription | Type: HUMAN PRESCRIPTION DRUG LABEL
Date: 20140502

ACTIVE INGREDIENTS: VITAMIN A ACETATE 2000 [iU]/1 1; .ALPHA.-TOCOPHEROL ACETATE 30 [iU]/1 1; ASCORBIC ACID 500 mg/1 1; THIAMINE MONONITRATE 20 mg/1 1; RIBOFLAVIN 20 mg/1 1; NIACINAMIDE 100 mg/1 1; PYRIDOXINE HYDROCHLORIDE 25 mg/1 1; BIOTIN 150 ug/1 1; CALCIUM PANTOTHENATE 25 mg/1 1; FOLIC ACID 1 mg/1 1; CYANOCOBALAMIN 50 ug/1 1; FLAVONE 50 mg/1 1; FERROUS FUMARATE 27 mg/1 1; CHROMIC CHLORIDE CR-51 0.1 mg/1 1; MAGNESIUM OXIDE 50 mg/1 1; MANGANESE GLUCONATE 5 mg/1 1; CUPRIC OXIDE 3 mg/1 1; SELENOMETHIONINE 50 ug/1 1; ZINC OXIDE 22.5 mg/1 1
INACTIVE INGREDIENTS: cellulose, microcrystalline; silicon dioxide; stearic acid; croscarmellose sodium; magnesium stearate; hypromelloses; maltodextrin; hydroxypropyl cellulose (type h); FD&C red No. 40; aluminum oxide; triacetin; titanium dioxide; polyethylene glycols; FD&C blue No. 1

BACMIN

Vitamin/Mineral Nutritional Supplement
Rx ONLY

DESCRIPTION

Each BACMIN caplet contains:

Quantity
Fat-Soluble Vitamins
Vitamin A (vitamin A acetate) | 2000 IU
Vitamin E (d-alpha tocopheryl acetate) | 30 IU
Water-Soluble Vitamins
Vitamin C (ascorbic acid) | 500 mg
Vitamin B1 (thiamine mononitrate) | 20 mg
Vitamin B2 (riboflavin) | 20 mg
Niacin (niacinamide) | 100 mg
Vitamin B6 (pyridoxine HCl) | 25 mg
Biotin | 150 mcg
Pantothenic acid (D-calcium pantothenate) | 25 mg
Folic acid | 1.0 mg
Vitamin B12 (cyanocobalamin) | 50 mcg
Lemon Bioflavonoids | 50 mg
Minerals
Iron (ferrous fumarate) | 27 mg
Chromium (chromium chloride) | 0.1 mg
Magnesium (magnesium oxide) | 50 mg
Manganese (manganese gluconate) | 5 mg
Copper (cupric oxide) | 3 mg
Selenium (L-selenomethionine) | 50 mcg
Zinc (zinc oxide) | 22.5 mg

DESCRIPTION

BACMIN is a prescription-only oral multivitamin/mineral caplet specially formulated for prophylactic or therapeutic nutritional supplementation in physiologically stressful conditions.

BACMIN supplies: therapeutic levels of water-soluble vitamins (ascorbic acid and all B-complex vitamins except biotin); supplemental levels of biotin, fat-soluble vitamins (A and E) and minerals (iron, chromium, manganese, copper, selenium and zinc); plus magnesium.

Inactive ingredients: microcrystalline cellulose, silicon dioxide, stearic acid, croscarmellose sodium and magnesium stearate. Coating contains: hydroxypropyl methylcellulose, maltodextrin, hydroxypropyl cellulose, FD&C red No. 40 aluminum lake, triacetin, titanium dioxide, polyethylene glycol, FD&C blue No. 1 aluminum lake.

INDICATIONS

BACMIN is indicated for prophylactic or therapeutic nutritional supplementation in physiologically stressful conditions. These include:

Conditions causing depletion, reduced absorption or bioavailability of essential vitamins and minerals-

- Inadequate intake due to highly restricted or unbalanced diets such as those frequently associated with anorexic conditions and other states of severe malnutrition.
- Gastrointestinal disorders, chronic alcoholism, chronic or acute infections (especially those involving febrile illness), prolonged or wasting disease, congestive heart failure, hyperthyroidism, poorly controlled diabetes or other physiologic stress.
- Also, patients on estrogenic oral contraceptives or other estrogen therapy, anti-bacterials which affect intestinal microflora, or other interfering drugs.

Certain conditions resulting from severe B-Vitamin or ascorbic acid deficiency-

- Recovery from surgery or trauma involving severe burns, fractures or other extensive tissue damage.
- Also, pregnant women and those with heavy menstrual bleeding.

CONTRAINDICATIONS

BACMIN is contraindicated in patients hypersensitive to any of its components.

WARNINGS

Not intended for treatment of pernicious anemia or other megaloblastic anemias where vitamin B12 is deficient. Neurological involvement may develop or progress, despite temporary remission of anemia, in patients with vitamin B12 deficiency who receive supplemental folic acid and who are inadequately treated with B12.

Drug and Treatment Interactions

As little as 5 mg pyridoxine daily can decrease the efficiency of levodopa in the treatment of parkinsonism. Therefore, BACMIN is not recommended for patients undergoing such therapy.

ADVERSE REACTIONS

Adverse reactions have been reported with specific vitamins and minerals, but generally at levels substantially higher than those in BACMIN. However, allergic and idiosyncratic reactions are possible at lower levels. Iron, even at the usual recommended levels, has been associated with gastrointestinal intolerance in some patients.

DOSAGE AND ADMINISTRATION

Usual adult dosage: one caplet daily.

HOW SUPPLIED

Dark red caplets. Bottles of 30, NDC 0682-3001-30. Bottles of 100, NDC 0682-3001-01.

Sample envelope - 2 caplets- NDC 0682-3001-02.

Imprint MMD on top with plain lower.

Manufactured for:
Marnel Pharmaceuticals,
Lafayette, LA 70506

Manufactured by:
Nexgen Pharma, Inc.,
Irvine, CA 92614

6381
Rev. 08/07B

PRINCIPAL DISPLAY PANEL - 100 Caplet Bottle Label

MARNEL

NDC 0682-3001-01

BACMIN
CAPLETS
VITAMIN/MINERAL NUTRITIONAL
SUPPLEMENT

Rx ONLY

100 CAPLETS

Manufactured for:
MARNEL PHARMACEUTICALS, INC.
Lafayette, Louisiana 70506